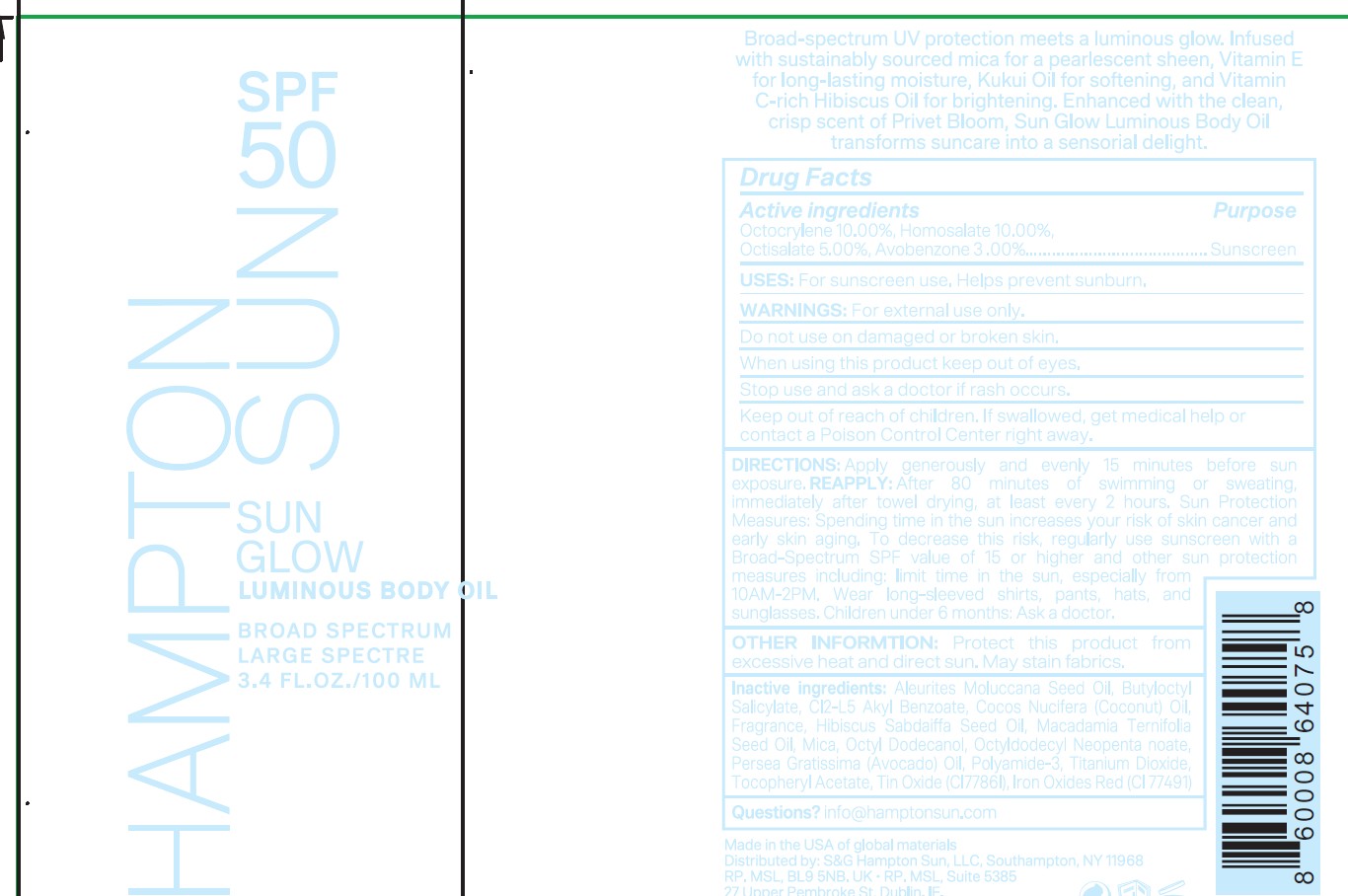 DRUG LABEL: HAMPTON SUN SPF50 SUNSHIELD BODY GLOW
NDC: 87170-010 | Form: OIL
Manufacturer: S&C Hampton Sun LLC
Category: otc | Type: HUMAN OTC DRUG LABEL
Date: 20260202

ACTIVE INGREDIENTS: HOMOSALATE 10 g/100 mL; OCTOCRYLENE 10 g/100 mL; AVOBENZONE 3 g/100 mL; OCTISALATE 5 g/100 mL
INACTIVE INGREDIENTS: KUKUI NUT OIL; BUTYLOCTYL SALICYLATE; C12-15 ALKYL BENZOATE; COCOS NUCIFERA (COCONUT) OIL; FRAGRANCE FLORAL ORC0902236; HIBISCUS SABDARIFFA SEED OIL; MACADAMIA TERNIFOLIA SEED OIL; MICA; OCTYLDODECANOL; OCTYLDODECYL NEOPENTANOATE; AVOCADO OIL; POLYAMIDE-3 (30000 MW); TITANIUM DIOXIDE; .ALPHA.-TOCOPHEROL ACETATE; TIN OXIDE; BROWN IRON OXIDE

HAMPTON SUN SPF50 SUNSHIELD BODY GLOW OIL (IS0397-HS)

Actove Ingredeints Purpose

Homosalate 10% Sunscreen

Octoclylene 10% Sunscreen

Avobenzone 3% Sunscreen

Octisalate 5% Sunscreen

Uses

Uses ■ helps prevent sunburn

DOSAGE AND ADMINISTRATION

Directionsapply liberally to cool, dry skin
15 minutes before sun exposure • reapply:
• after 80 minutes of swimming or sweating
• immediately after towel drying • at least every 2
hours • Sun Protection Measures. Spending time
in the sun increases your risk of skin cancer and
early skin aging. To decrease this risk, regularly
use a sunscreen with a broad spectrum SPF of 15
or higher and other sun protection measures
including: • limit time in the sun,especially from
10 a.m. - 2. p.m. • wear a long-sleeve shirts,
pants, hats, and sunglasses. • children under 6
months: Ask a doctor.

Warnings

For external use only.
Do not useon damaged or broken skin.
When using this product■ keep out of eyes. Rinse eyes with water to remove.
Stop use and ask a doctor ifrash occurs.

Keep out of reach of children.if swallowed, get medical
help or contact a Polson Control Center right away.

Inactive Ingredients

Aleurites Moluccana Seed Oil,
Butyloctyl Salicylate
C12-15 Akyl Benzoate
Cocos Nucifera (Coconut) Oil
Fragrance
Hibiscus Sabdaiffa Seed Oil
Macadamia Ternifolia Seed Oil,
Mica
Octyl Dodecanol
Octyldodecyl Neopentanoate
Persea Gratissima (Avocado) Oil
Polyamide-3
Titanium Dioxide
Tocopheryl Acetate
Tin Oxide (CI77861)
Iron Oxide Red (CI 77491)
Iron Oxides Red (CI 77491)